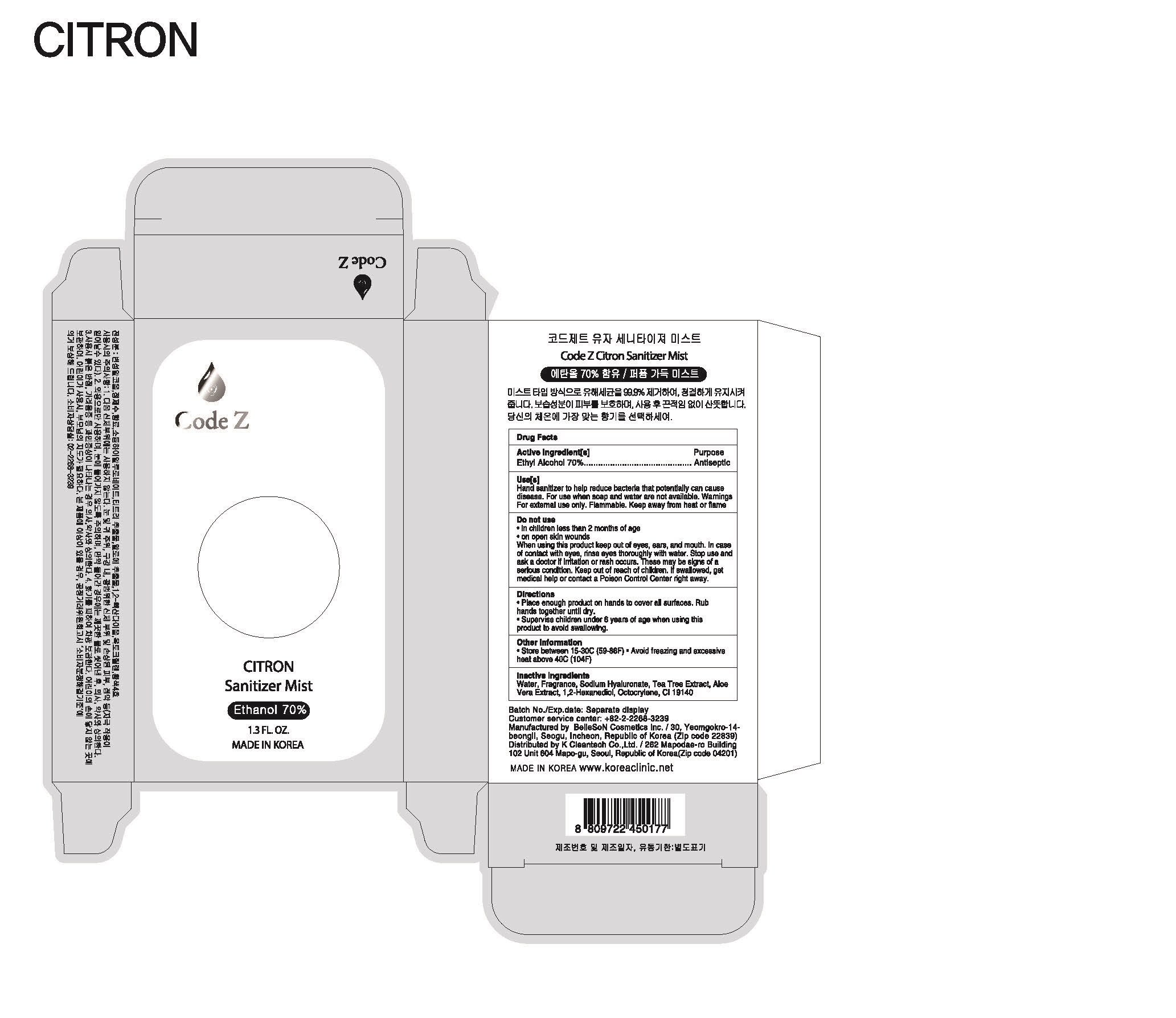 DRUG LABEL: Code Z Citron Sanitizer Mist
NDC: 80079-0002 | Form: LIQUID
Manufacturer: K CLEANTECH CO., LTD.
Category: otc | Type: HUMAN OTC DRUG LABEL
Date: 20200817

ACTIVE INGREDIENTS: ALCOHOL 70 mL/100 mL
INACTIVE INGREDIENTS: WATER; ALOE VERA LEAF; 1,2-HEXANEDIOL; FD&C YELLOW NO. 5; OCTOCRYLENE; HYALURONATE SODIUM; TEA TREE OIL

Drug Facts

ACTIVE INGREDIENT

alcohol

INACTIVE INGREDIENT

WATER, fragrance, sodium hyaluronate, aloe vera extract, 1,2-hexanediol, octocrylene, CI 1914

PURPOSE

■ instant healthcare personnel hand antiseptic to reduce bacteria that potentially can cause disease

■ instant hand antiseptic to decrease bacteria on the skin

KEEP OUT OF REACH OF THE CHILDREN

INDICATIONS AND USAGE

Apply an appropriate amount on your hands and rub well until dry.

WARNINGS

1. Do not use on the following body parts. A wide range of body parts and damaged skin around the eyes and ears, in the oral cavity (may have irritating effects)
2. If the following symptoms appear, stop using them immediately and consult a doctor or pharmacist.
1) Hypersensitivity symptoms such as rash, erythema, itching, and edema
2) Skin irritation symptoms

DOSAGE AND ADMINISTRATION

for external use only